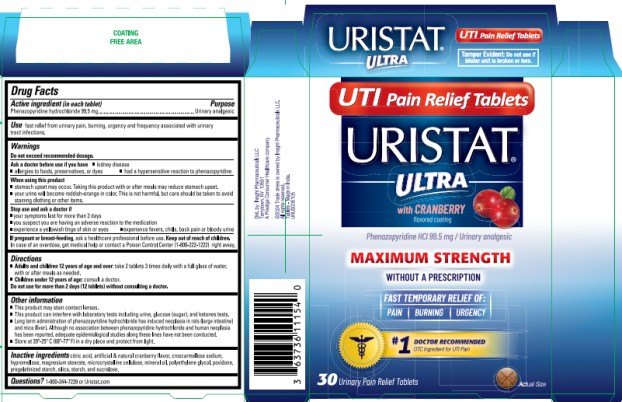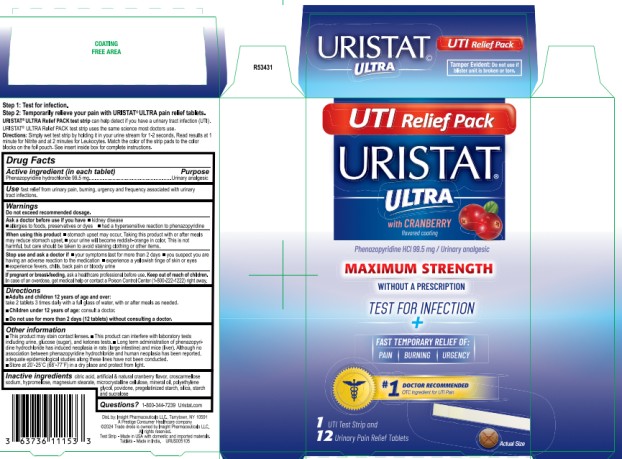 DRUG LABEL: Uristat Ultra
NDC: 63029-105 | Form: TABLET
Manufacturer: Medtech Products Inc.
Category: otc | Type: HUMAN OTC DRUG LABEL
Date: 20251023

ACTIVE INGREDIENTS: PHENAZOPYRIDINE HYDROCHLORIDE 99.5 mg/1 1
INACTIVE INGREDIENTS: CITRIC ACID MONOHYDRATE; CROSCARMELLOSE SODIUM; HYPROMELLOSES; MAGNESIUM STEARATE; CELLULOSE, MICROCRYSTALLINE; MINERAL OIL; POLYETHYLENE GLYCOL, UNSPECIFIED; POVIDONE; SILICON DIOXIDE; STARCH, CORN; SUCRALOSE

Uristat Ultra

URISTAT ® ULTRA

Phenazopyridine Hydrochloride 99.5 mg

Drug Facts

Active ingredient (in each tablet)

Phenazopyridine hydrochloride 99.5 mg

Purpose

Urinary analgesic

Use

fast relief from urinary pain, burning, urgency and frequency associated with urinary tract infections

Warnings

Do not exceed recommended dosage

Ask a doctor before use if you have

- kidney disease
- allergies to foods, preservatives, or dyes
- had a hypersensitive reaction to phenazopyridine

When using this product

- stomach upset may occur. Taking this product with or after meals may reduce stomach upset
- your urine will become reddish-orange in color. This is not harmful, but care should be taken to avoid staining clothing or other items.

Stop use and ask a doctor if

- your symptoms last for more than 2 days
- you suspect you are having an adverse reaction to the medication
- experience a yellowish tinge of skin or eyes
- experience fevers chills, back pain or bloody urine

If pregnant or breast-feeding,

ask a health care professional before use.

Keep out of reach of children.

In case of an overdose, get medical help or contact a Poison Control Center (1-800-222-1222) right away.

Directions

- Adults and children 12 years of age and over: take 2 tablets 3 times daily with a full glass of water, with or after meals as needed
- Children under 12 years of age: consult a doctor.
- Do not use for more than 2 days (12 tablets) without consulting a doctor

Other information

- This product may stain contact lenses
- This product can interfere with laboratory tests including urine, glucose (sugar), and ketones test
- Long term administration of phenazopyridine HCl has induced neoplasia in rats (large intestine) and mice (liver). Although no association between phenazopyridine hydrochloride and human neoplasia has been reported, adequate epidemiological studies along these lines have not been conducted
- Store at 20º-25º C (68º-77º F) in a dry place and protect from light.

Inactive ingredients

citric acid, artificial & natural cranberry flavor, croscarmellose sodium, hypromellose, magnesium stearate, microcrystalline cellulose, mineral oil, polyethylene glycol, povidone, pregelatinized starch, silica, starch, and sucralose.

Questions?

1-800-344-7239 Uristat.com

PRINCIPAL DISPLAY PANEL

URISTAT® ULTRA with Cranberry flavored coating

UTI Pain Relief Tablets

Phenazopyridine Hydrochloride 99.5 mg

30 Urinary Pain Relief Tablets

PRINCIPAL DISPLAY PANEL

RISTAT® ULTRA with Cranberry flavored coating

UTI Relief PAK™

Phenazopyridine Hydrochloride 99.5 mg

1 UTI Test Strip and 12 Urinary Pain Relief Tablets